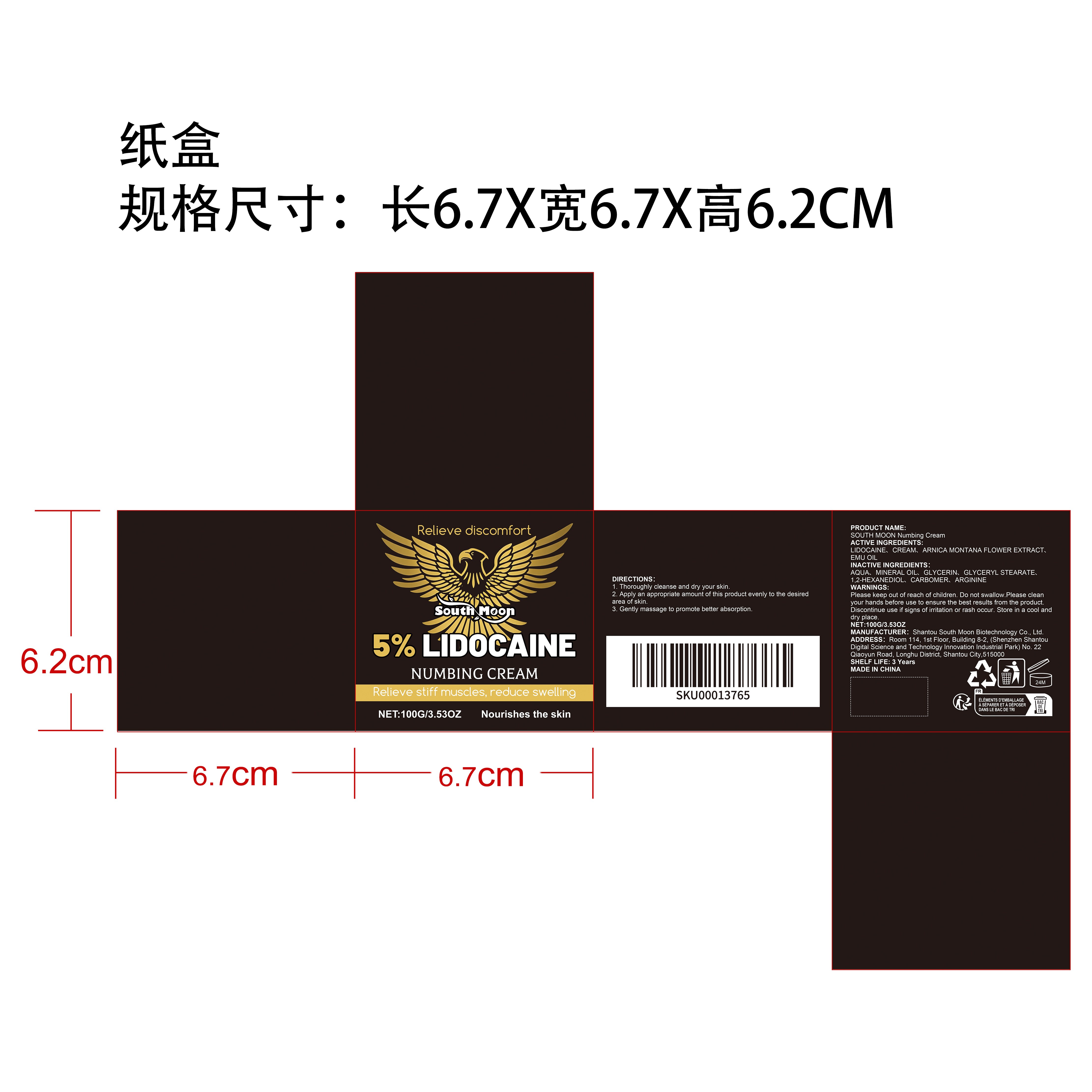 DRUG LABEL: SOUTH MOON Numbing Cream
NDC: 84983-022 | Form: CREAM
Manufacturer: Shantou South Moon Biotechnology Co., Ltd.
Category: otc | Type: HUMAN OTC DRUG LABEL
Date: 20260202

ACTIVE INGREDIENTS: EMU OIL 0.01 mg/100 mg; CREAM 0.01 mg/100 mg; ARNICA MONTANA FLOWER 0.01 mg/100 mg; LIDOCAINE 5 mg/100 mg
INACTIVE INGREDIENTS: GLYCERIN 5 mg/100 mg; GLYCERYL STEARATE 1 mg/100 mg; MINERAL OIL 5 mg/100 mg; CARBOMER 0.3 mg/100 mg; 1,2-HEXANEDIOL 0.5 mg/100 mg; AQUA 82.87 mg/100 mg; ARGININE 0.3 mg/100 mg

ACTIVE INGREDIENT

LIDOCAINE、CREAM、ARNICA MONTANA FLOWER EXTRACT、EMU OIL

PURPOSE

1. Helps soothe skin, reduce acne redness and swelling, eliminate skin blemishes, and keep your facial skin soft. 2. It can provide moisturizing effect to the skin, moisturize the skin, and keep your skin hydrated. 3. It has a light texture and can be quickly absorbed by the skin, leaving it refreshing and non-greasy after use.

WHEN USING

1. Thoroughly cleanse and dry your skin.
2. Apply an appropriate amount of this product evenly to the desired area of skin.
3. Gently massage to promote better absorption.

WARNINGS

Please keep out of reach of children. Do not swallow.Please clean your hands before use to ensure the best results from the product. Discontinue use if signs of irritation or rash occur. Store in a cool and dry place.

DO NOT USE

Discontinue use if signs of irritation or rash occur.

STOP USE

Discontinue use if signs of irritation or rash occur.

KEEP OUT OF REACH OF CHILDREN

Please keep out of reach of children. Do not swallow.

STORAGE AND HANDLING

Store in a cool and dry place.

INACTIVE INGREDIENT

AQUA、MINERAL OIL、GLYCERIN、GLYCERYL STEARATE、1,2-HEXANEDIOL、CARBOMER、ARGININE

INDICATIONS AND USAGE

1. Thoroughly cleanse and dry your skin.
2. Apply an appropriate amount of this product evenly to the desired area of skin.
3. Gently massage to promote better absorption.

DOSAGE AND ADMINISTRATION

1. Thoroughly cleanse and dry your skin.
2. Apply an appropriate amount of this product evenly to the desired area of skin.
3. Gently massage to promote better absorption.